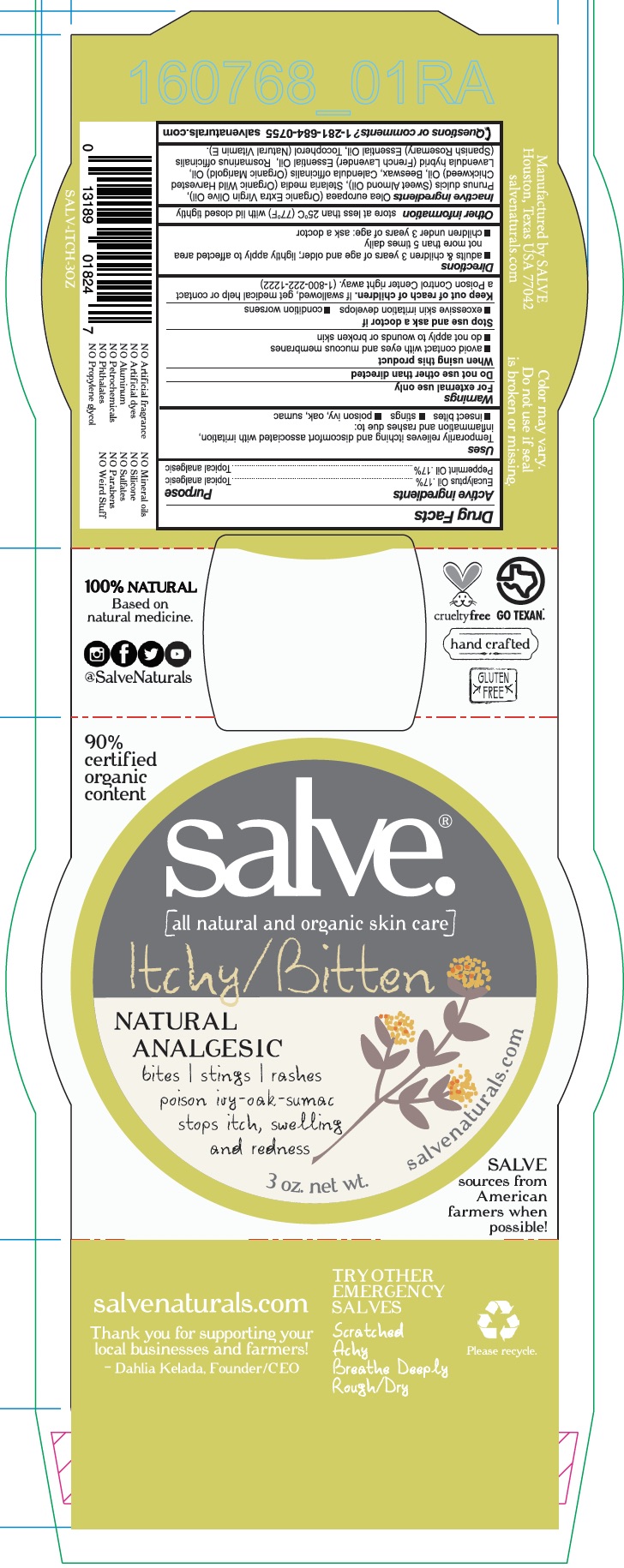 DRUG LABEL: Itchy Bitten
NDC: 71157-0018 | Form: GEL
Manufacturer: Kelada Creative Group
Category: homeopathic | Type: HUMAN OTC DRUG LABEL
Date: 20171016

ACTIVE INGREDIENTS: PEPPERMINT OIL 3 g/90 mL; CORYMBIA CITRIODORA LEAF OIL 3 g/90 mL
INACTIVE INGREDIENTS: STELLARIA MEDIA LEAF; WHITE WAX; LAVENDER OIL; ROSEMARY OIL; OLIVE OIL; CALENDULA OFFICINALIS FLOWER; .ALPHA.-TOCOPHEROL; ALMOND OIL

Itchy/Bitten

ACTIVE INGREDIENT

Eucalyptus Oil .17%

Peppermint Oil.17%

PURPOSE

Temporarily relieves itching and discomfort associated with irritation, inflammation, and rashes due to insect bites, stings, poison ivy, oak and sumac

WARNINGS

For external use only

Do not use other than as directed

When using this product

- avoid contact with eyes and mucous membranes
- do not apply to wounds or broken skin

INDICATIONS AND USAGE

Temporarily relieves itching and discomfort associated with irritation, inflammation, and rashes due to insect bites, stings, poison ivy, oak and sumac

Keep out of reach of children. If swallowed, get medical help or contact Poison Control Center right away.

INACTIVE INGREDIENT

Organic Extra Virgin Olive Oil, Sweet Almond Oil, Organic Wild Harvested Chickweed Oil, Beeswax, Organic Marigold Oil, French Lavender Essential Oil, Spanish Rosemary Essential Oil, Natural Vitamin E.

DOSAGE AND ADMINISTRATION

- Adults and children 3 years of age and older; lightly apply to affected area not more than 5 times daily
- Children under 3 years of age; ask a doctor